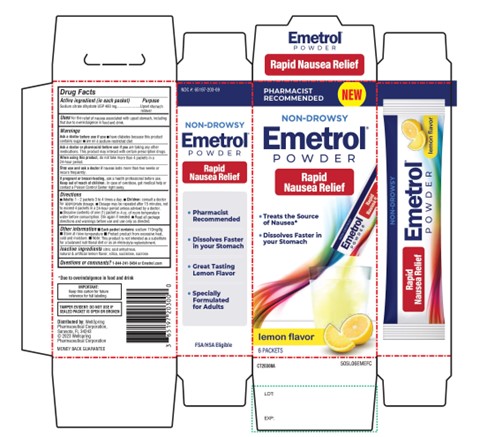 DRUG LABEL: Emetrol Powder
NDC: 65197-203 | Form: POWDER, FOR SOLUTION
Manufacturer: WellSpring Pharmaceutical Corporation
Category: otc | Type: HUMAN OTC DRUG LABEL
Date: 20250108

ACTIVE INGREDIENTS: TRISODIUM CITRATE DIHYDRATE 460 mg/1 1
INACTIVE INGREDIENTS: ANHYDROUS CITRIC ACID; LEMON; SILICON DIOXIDE; SUCRALOSE; SUCROSE

Emetrol Non-Drowsy Powder Rapid Nausea Relief

Active ingredients (in each packet)

- Sodium citrate dihydrate USP 460 mg

Purpose

Upset stomach reliever

Uses

For the relief of nausea associated with upset stomach, including that due to overindulgence in food and drink.

Warnings

Ask a doctor before use if you

- have diabetes because this product contains sugar
- are on a sodium-restricted diet

Ask a doctor or pharmacist before use if

- you are taking any other medications. This product may interact with certain prescription drugs.

When using this product,

- do not take more than 4 packets in a 24-hour period.

Stop use and ask a doctor if

- nausea lasts more than two weeks or recurs frequently.

If pregnant or breast-feeding,

- ask a health professional before use.

Keep out of reach of children

In case of overdose, get medical help or contact a Poison Control Center right away.

Directions

- Adults: 1-2 packets 3 to 4 times a day.
- Children: Consult a doctor for appropriate dosage.
- Dosage may be repeated after 15 minutes, not to exceed 4 packets in a 24-hour period unless advised by a doctor.
- Dissolve contents of one (1) packet in 4 oz. of room temperature water before consumption. Stir again if needed
- Read all package directions and warnings before use and use only as directed.

Other information

- Each table contains: Sodium 110 mg/8 g
- Store at room temperature
- Protect product from excessive heat, cold and moisture.
- Note: This product is not intended as a substitute for a balanced nutritional diet or as an electrolyte replenishment.

Inactive ingredients

Citric acid anhydrous, natural & artificial lemon flavor, silica, sucralose, sucrose.

Questions or Comments?

1-844-241-5454 or Emetrol.com

Distributed By

WellSpring Pharmaceutical Corporation
Sarasota, FL 34243
(c) 2023 WellSpring Pharmaceutical Corporation

PACKAGE LABEL

PHARMACIST RECOMMENDED

NDC# 65197-203-09

New

Non-Drowsy

Emetrol POWDER

Rapid Nausea Relief

- Treats the source of Nausea*
- Dissolve Faster in your Stomach
- Great Tasting Lemon Flavor
- Specially Formulated for Adults

*Due to overindulgence in food and drink

FSA/HAS Eligible

lemon flavor

6 PACKAETS